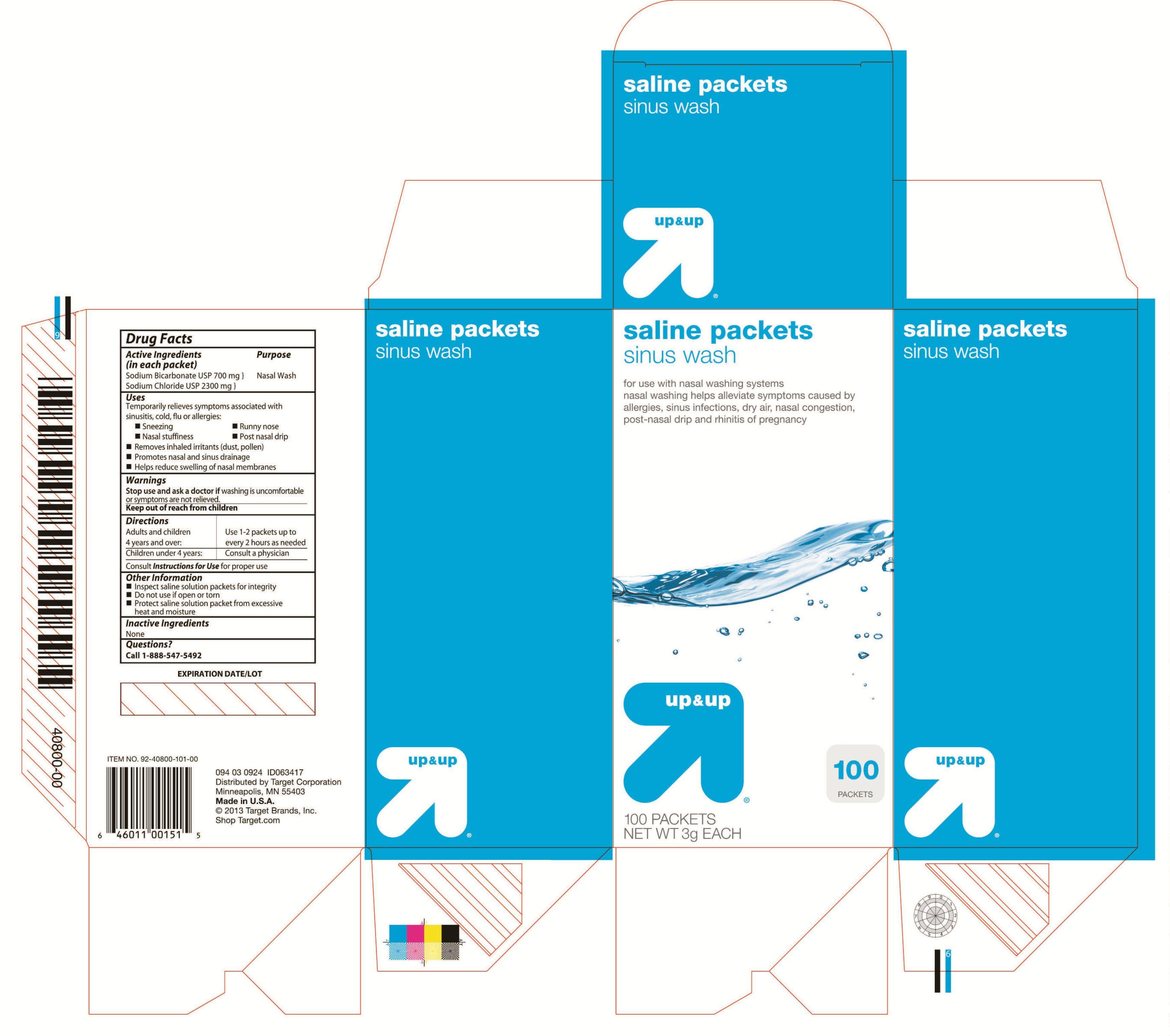 DRUG LABEL: Saline Wash
NDC: 11673-408 | Form: POWDER, FOR SOLUTION
Manufacturer: Target Corporation
Category: otc | Type: HUMAN OTC DRUG LABEL
Date: 20130522

ACTIVE INGREDIENTS: SODIUM CHLORIDE 700 mg/1 1; SODIUM BICARBONATE 2300 mg/1 1

Drug Facts

Inactive Ingredients

None

Active Ingredients

(in each packet)

Sodium Bicarbonate USP 700 mg

Sodium Chloride USP 1200 mg

Warnings

For external use only

Purpose

Nasal wash

Keep out of reach from children

Uses

Temporarily relieves symptoms associated with sinusitis, colds, flu or allergies

Sneezing

Runny nose

Nasal stuffiness

Post nasal drip

Removes inhaled irritants (dust, pollen)

Promotes nasal and sinus drainage

Helps reduce swelling of nasal membranes

Directions

Adults and children 4 years and over: 1-2 packets every 2 hours as needed

Children under 4 years: Consult a doctor

Consult Instructions for Use for proper use

Other Information

Inspect saline solution packets for integrity

Do not use if open or torn

Protect saline solution packets from excessive heat and moisture